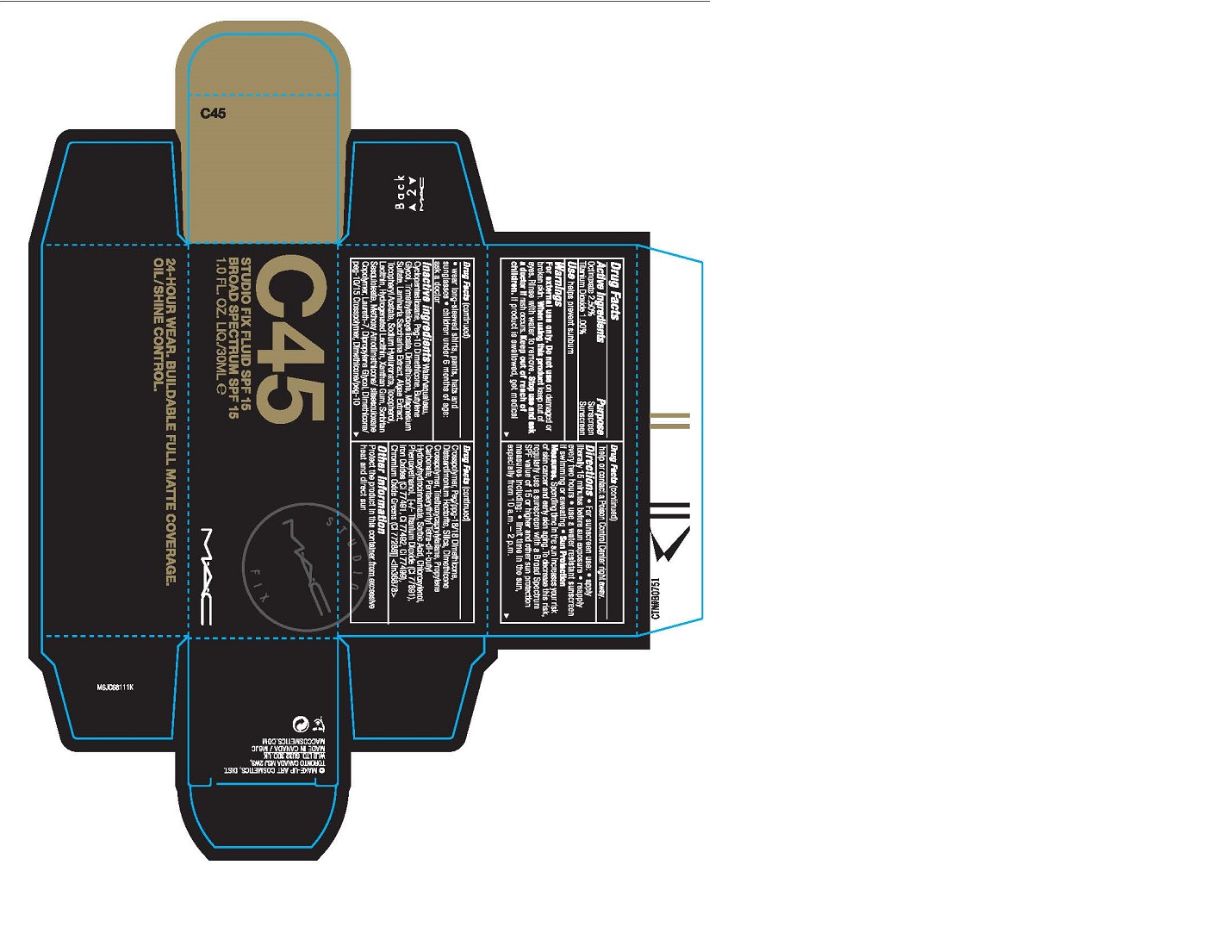 DRUG LABEL: STUDIO FIX FLUID SPF 15 BROAD SPECTRUM
NDC: 40046-0072 | Form: LIQUID
Manufacturer: MAKEUP ART COSMETICS
Category: otc | Type: HUMAN OTC DRUG LABEL
Date: 20241225

ACTIVE INGREDIENTS: OCTINOXATE 25 mg/1 mL; TITANIUM DIOXIDE 10 mg/1 mL
INACTIVE INGREDIENTS: WATER; CYCLOMETHICONE 5; BUTYLENE GLYCOL; DIMETHICONE; MAGNESIUM SULFATE, UNSPECIFIED FORM; SACCHARINA LATISSIMA; .ALPHA.-TOCOPHEROL ACETATE; HYALURONATE SODIUM; TOCOPHEROL; XANTHAN GUM; SORBITAN SESQUIOLEATE; LAURETH-7; DIPROPYLENE GLYCOL; PEG/PPG-18/18 DIMETHICONE; DISTEARDIMONIUM HECTORITE; SILICON DIOXIDE; TRIETHOXYCAPRYLYLSILANE; PROPYLENE CARBONATE; PENTAERYTHRITOL TETRAKIS(3-(3,5-DI-TERT-BUTYL-4-HYDROXYPHENYL)PROPIONATE); SORBIC ACID; CHLOROXYLENOL; PHENOXYETHANOL; FERRIC OXIDE RED; FERRIC OXIDE YELLOW; FERROSOFERRIC OXIDE; CHROMIC OXIDE

STUDIO FIX FLUID SPF 15 BROAD SPECTRUM

Drug Facts

ACTIVE INGREDIENT

Active Ingredients | Purpose
Octinoxate 2.50% | Sunscreen
Titanium Dioxide 1.00% | Sunscreen

Use

helps prevent sunburn

Warnings

For external use only

Do not use on damaged or broken skin

When using this product keep out of eyes. Rinse with water to remove.

Stop use and ask a doctor if rash occurs

Keep out of reach of children. If product is swallowed, get medical help or contact a Poison Control Center right away.

Directions

For sunscreen use:

- apply liberally 15 minutes before sun exposure
- reapply every two hours
- use a water resistant sunscreen if swimming or sweating
- Sun Protection Measures. Spending time in the sun increases your risk of skin cancer and early skin aging. To decrease this risk, regularly use a sunscreen with a Broad Spectrum SPF value of 15 or higher and other sun protection measures including:
  - limit time in the sun, especially from 10 a.m. - 2 p.m.
  - wear long-sleeved shirts, pants, hats and sunglasses
- children under 6 months of age: ask a doctor

inactive ingredients

water/aqua/eau, cyclopentasiloxane, peg-10 dimethicone, butylene glycol, trimethylsiloxysilicate, dimethicone, magnesium sulfate, laminaria saccharina extract, algae extract, tocopheryl acetate, sodium hyaluronate, tocopherol, lecithin, hydrogenated lecithin, xanthan gum, sorbitan sesquioleate, methoxy amodimethicone/silsesquioxane copolymer, laureth-7, dipropylene glycol, dimethicone/peg-10/15 crosspolymer, dimethicone/peg-10 crosspolymer, peg/ppg-18/18 dimethicone, disteardimonium hectorite, silica, dimethicone crosspolymer, triethoxycaprylylsilane, propylene carbonate, pentaerythrityl tetra-di-t-butyl hydroxyhydrocinnamate, sorbic acid, chloroxylenol, phenoxyethanol [+/- titanium dioxide (ci 77891), iron oxides (ci 77491, ci 77492, ci 77499), chromium oxide greens (ci 77288)] <iln36878>

Other information

protect the product in this container from excessive heat and direct sun

DIST. BY: MAKE-UP ART COSMETICS
TORONTO, ONTARIO, CANADA M5V 1R7
LONDON W1K 3BQ / M6JC

PRINCIPAL DISPLAY PANEL - 30 ML Bottle Carton

M•A•C

STUDIO FIX FLUID
SPF 15
BROAD SPECTRUM SPF 15

30 ML/1.0 US FL OZ e